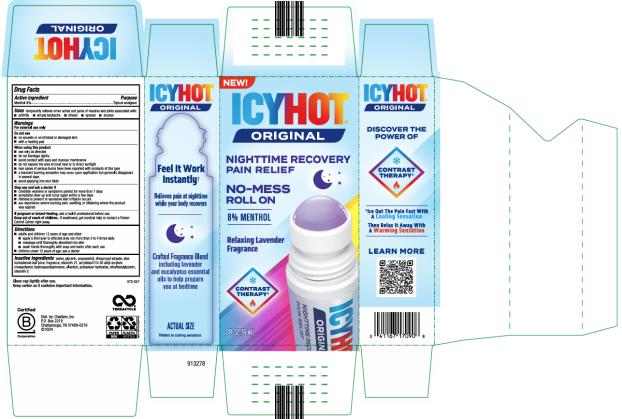 DRUG LABEL: Icy Hot Original Nighttime Recovery Pain Relief No Mess Roll On
NDC: 41167-1709 | Form: LIQUID
Manufacturer: Chattem, Inc.
Category: otc | Type: HUMAN OTC DRUG LABEL
Date: 20250110

ACTIVE INGREDIENTS: MENTHOL 8 g/100 mL
INACTIVE INGREDIENTS: WATER; GLYCERIN; PROPANEDIOL; DIISOPROPYL ADIPATE; ALOE BARBADENSIS LEAF; STEARETH-21; HYDROXYACETOPHENONE; ALLANTOIN; POTASSIUM HYDROXIDE; ETHYLHEXYLGLYCERIN; STEARETH-2; ACRYLATES/C10-30 ALKYL ACRYLATE CROSSPOLYMER (60000 MPA.S)

Icy Hot Original Nighttime Recovery Pain Relief No Mess Roll On

Icy Hot Original Nighttime Recovery Pain Relief No Mess Roll On

Drug Facts

Active ingredient

Menthol 8%

Purpose

Topical Analgesic

Use

temporarily relieves minor aches and pains of muscles and joints associated with: ■ arthritis ■ simple backache ■ strains ■ sprains ■ bruises

Warnings

For external use only

Do not use

■ on wounds or on irritated or damaged skin

■ with a heating pad

When using this product

■ use only as directed

■ do not bandage tightly

■ avoid contact with eyes and mucous membranes

■ do not expose the area to local heat or to direct sunlight

■ rare cases of serious burns have been reported with products of this type

■ a transient burning sensation may occur upon application but generally disappears in several days

■ avoid applying into skin folds

Stop use and ask a doctor if

■ condition worsens or symptoms persist for more than 7 days

■ symptoms clear up and occur again within a few days

■ redness is present or excessive skin irritation occurs

■ you experience severe burning pain, swelling, or blistering where the product was applied

Keep out of reach of children.

If swallowed, get medical help or contact a Poison Control Center right away.

Directions

■ adults and children 12 years of age and older:

■ apply a thin layer to affected area not more than 3 to 4 times daily

■ massage until thoroughly absorbed into skin

■ wash hands thoroughly with soap and water after each use

■ children under 12 years of age: ask a doctor

Inactive ingredients

water, glycerin, propanediol, diisopropyl adipate, aloe barbadensis leaf juice, fragrance, steareth-21, acrylates/C10-30 alkyl acrylate crosspolymer, hydroxyacetophenone, allantoin, potassium hydroxide, ethylhexylglycerin, steareth-2

PRINCIPAL DISPLAY PANEL

ICYHOT
ORIGINAL
NIGHTTIME RECOVERY
PAIN RELIEF
NO-MESS
ROLL ON